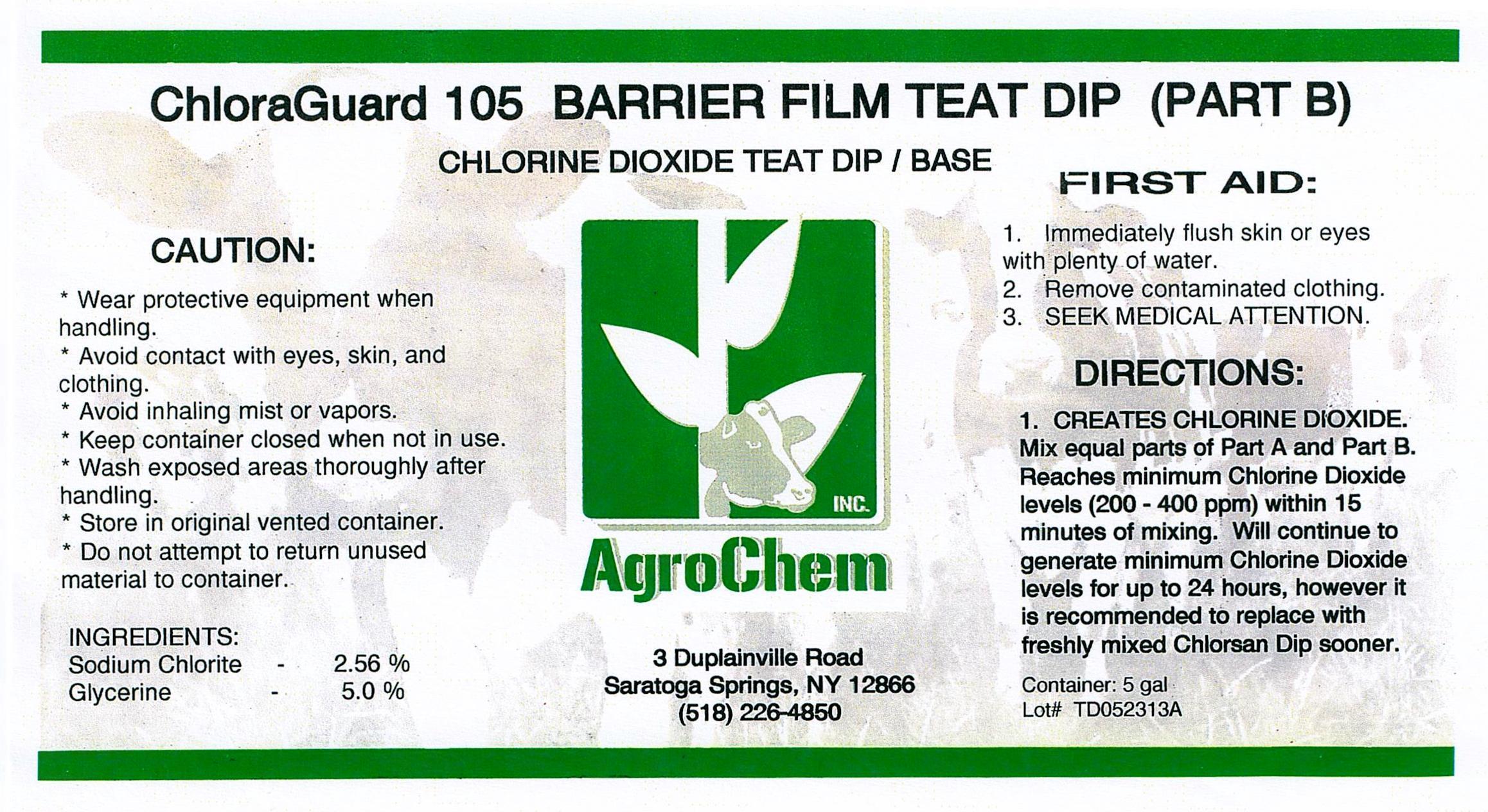 DRUG LABEL: ChloraGuard 105 Part B
NDC: 17307-3611 | Form: SOLUTION
Manufacturer: AgroChem Inc
Category: animal | Type: OTC ANIMAL DRUG LABEL
Date: 20131031

ACTIVE INGREDIENTS: SODIUM CHLORITE 0.0256 kg/1 kg
INACTIVE INGREDIENTS: POLYVINYL ALCOHOL 0.05 kg/1 kg; GLYCERIN 0.05 kg/1 kg; ALCOHOL 0.02 kg/1 kg

ChloraGuard 105 Part B

DESCRIPTION

CHLORINE DIOXIDE TEAT DIP/BASE

WARNINGS AND PRECAUTIONS

CAUTION:

* Wear protective equipment when

handling.

* Avoid contact with eyes, skin, and

clothing.

* Keep container closed when not in use.

* Wash exposed area thoroughly after

handling.

* Store in original vented container.

* Do not attempt to return unused material

to container.

ACTIVE INGREDIENT

INGREDIENTS:

Sodium Chlorite - 2.56%

Glycerine - 5.0%

WARNINGS AND PRECAUTIONS

FIRST AID:

1. Immediately flush skin or eyes with

plenty of water.

2. Remove contaminated clothing.

3. SEEK MEDICAL ATTENTION.

DIRECTIONS:

1. CREATES CHLORINE DIOXIDE.

Mix equal parts of Part A and Part

B. Reaches minimum Chlorine

Dioxide levels (200 - 400 ppm)

within 15 minutes of mixing. Will

continue to generate minimum

Chlorine Dioxide levels for up to 24

hours, however it is recommended

to replace with freshly mixed

Chlorsan Dip sooner.